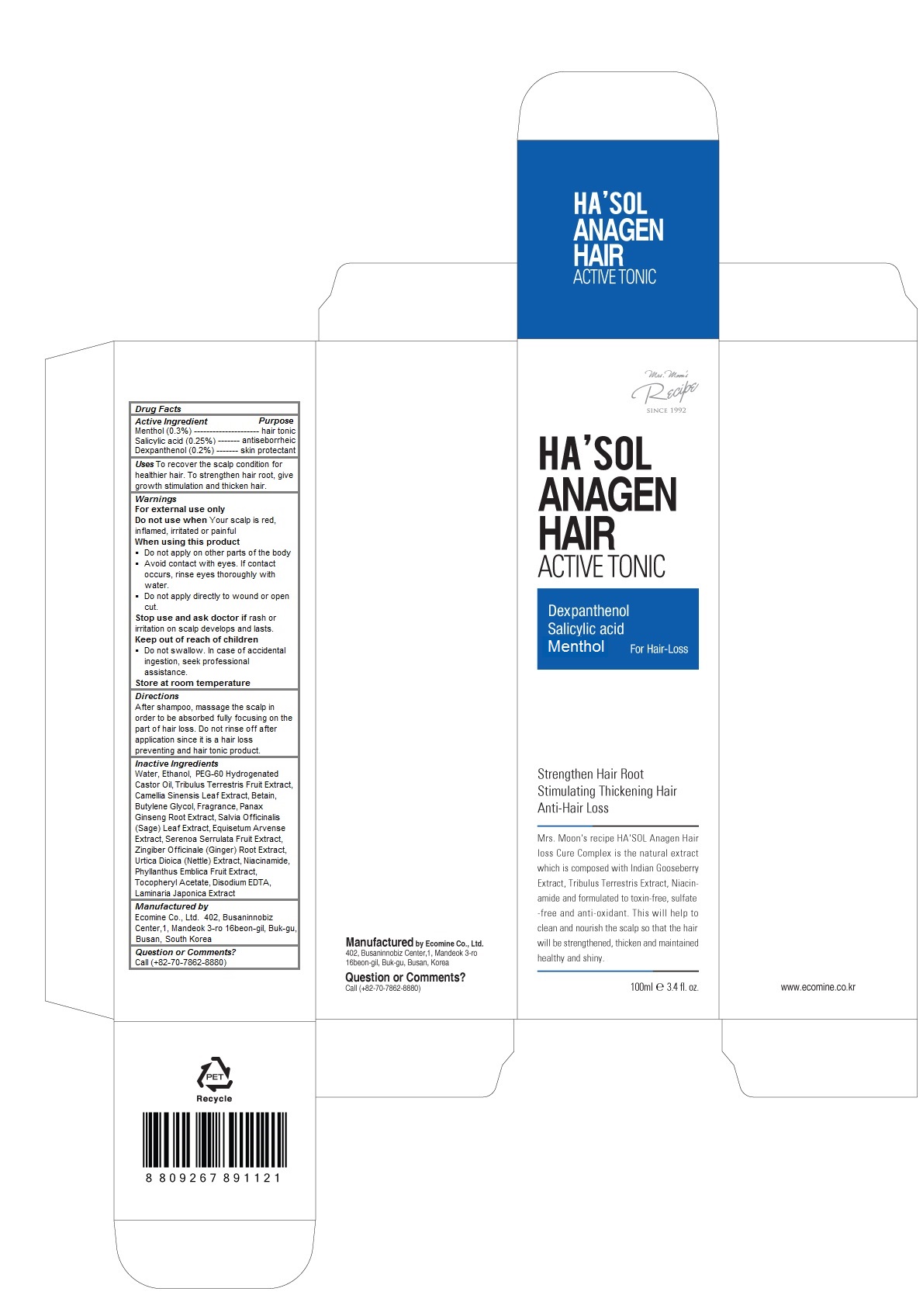 DRUG LABEL: HASOL Anagen Hair Tonic
NDC: 51270-122 | Form: LIQUID
Manufacturer: ECOMINE Co., Ltd.
Category: otc | Type: HUMAN OTC DRUG LABEL
Date: 20160407

ACTIVE INGREDIENTS: Dexpanthenol 0.002 1/100 mL; Menthol 0.003 1/100 mL; Salicylic Acid 0.0025 1/100 mL
INACTIVE INGREDIENTS: water; ALCOHOL; PEG-60 HYDROGENATED CASTOR OIL; TRIBULUS TERRESTRIS FRUIT; GREEN TEA LEAF; BETAINE; BUTYLENE GLYCOL; ASIAN GINSENG; SAGE; EQUISETUM ARVENSE BRANCH; SAW PALMETTO; GINGER; URTICA DIOICA LEAF; PHYLLANTHUS EMBLICA FRUIT; .ALPHA.-TOCOPHEROL ACETATE; EDETATE DISODIUM; LAMINARIA JAPONICA; Niacinamide

HA'SOL Anagen Hair Tonic